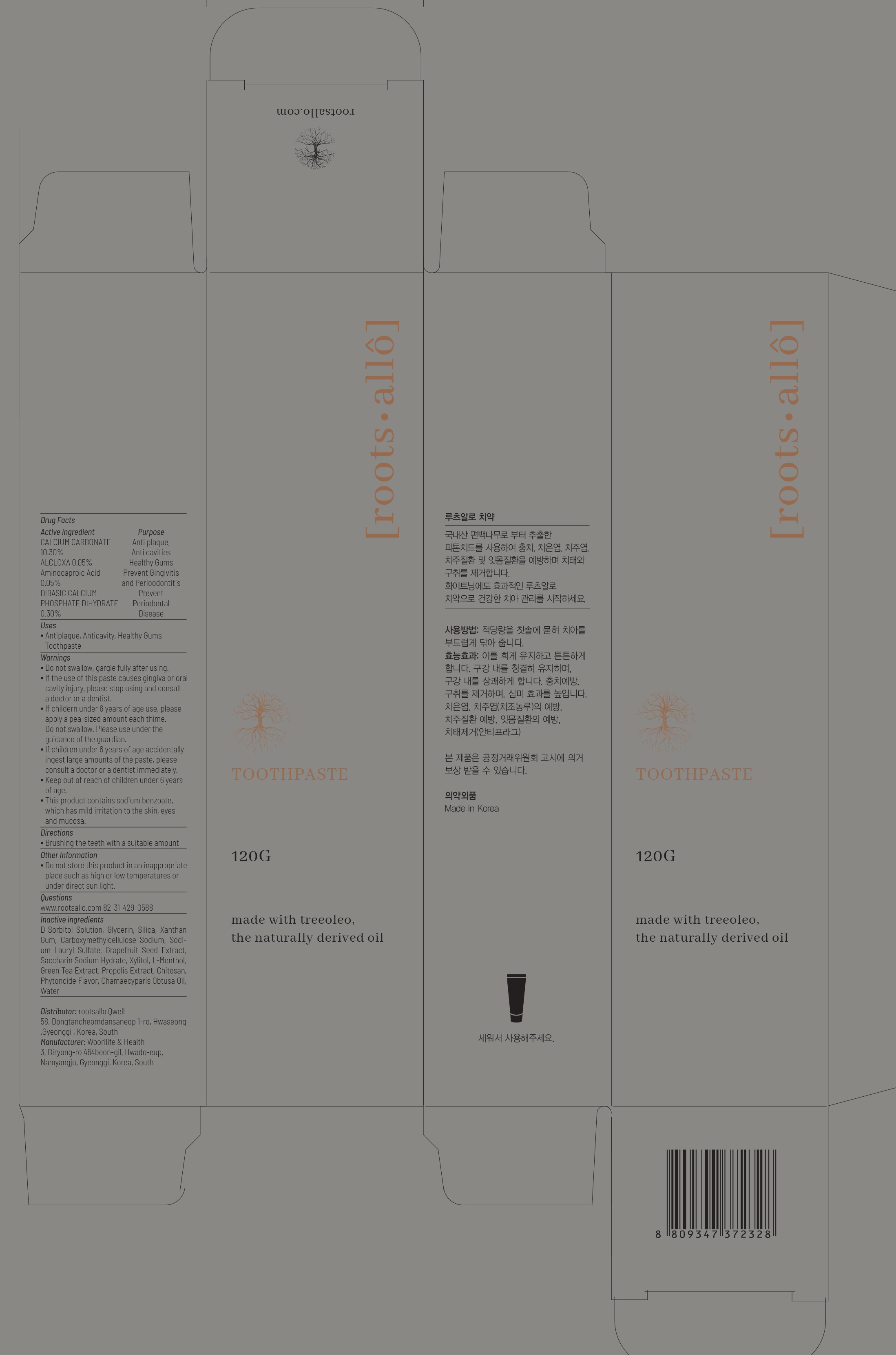 DRUG LABEL: ROOTSALLO TOOTHPASTE
NDC: 82450-050 | Form: GEL, DENTIFRICE
Manufacturer: rootsallo Qwell
Category: otc | Type: HUMAN OTC DRUG LABEL
Date: 20211230

ACTIVE INGREDIENTS: CALCIUM CARBONATE 10.30 g/100 g; ALCLOXA 0.05 g/100 g; Aminocaproic Acid 0.05 g/100 g; DIBASIC CALCIUM PHOSPHATE DIHYDRATE 0.30 g/100 g
INACTIVE INGREDIENTS: SORBITOL; Glycerin; SILICON DIOXIDE

ACTIVE INGREDIENTS

CALCIUM CARBONATE 10.30%
ALCLOXA 0.05%
Aminocaproic Acid 0.05%
DIBASIC CALCIUM PHOSPHATE DIHYDRATE 0.30%

PURPOSE

Anti plaque, Anti cavities, Healthy Gums, Prevent Gingivitis and Perioodontitis, Prevent Periodontal Disease

Uses

Antiplaque, Anticavity, Healthy Gums Toothpaste

Warnings

(1) Do not swallow, gargle fully after using.
(2) If the use of this paste causes gingiva or oral cavity injury, please stop using and consult a doctor or a dentist.
(3) If childern under 6 years of age use, please apply a pea-sized amount each thime.
Do not swallow. Please use under the guidance of the guardian.
(4) If children under 6 years of age accidentally ingest large amounts of the paste, please consult a doctor or a dentist immediately.
(5) Keep out of reach of children under 6 years of age.
(6) This product contains sodium benzoate, which has mild irritation to the skin, eyes and mucosa.

Keep out of reach of children under 6 years of age.

Directions

Brushing the teeth with a suitable amount

Other Information

Do not store this product in an inappropriate place such as high or low temperatures or under direct sun light.

Questions

www.rootsallo.com 82-31-429-0588

Inactive ingredients

D-Sorbitol Solution, Glycerin, Silica, Xanthan Gum, Carboxymethylcellulose Sodium, Sodium Lauryl Sulfate, Grapefruit Seed Extract, Saccharin Sodium Hydrate, Xylitol, L-Menthol, Green Tea Extract, Propolis Extract, Chitosan, Phytoncide Flavor, Chamaecyparis Obtusa Oil, Water